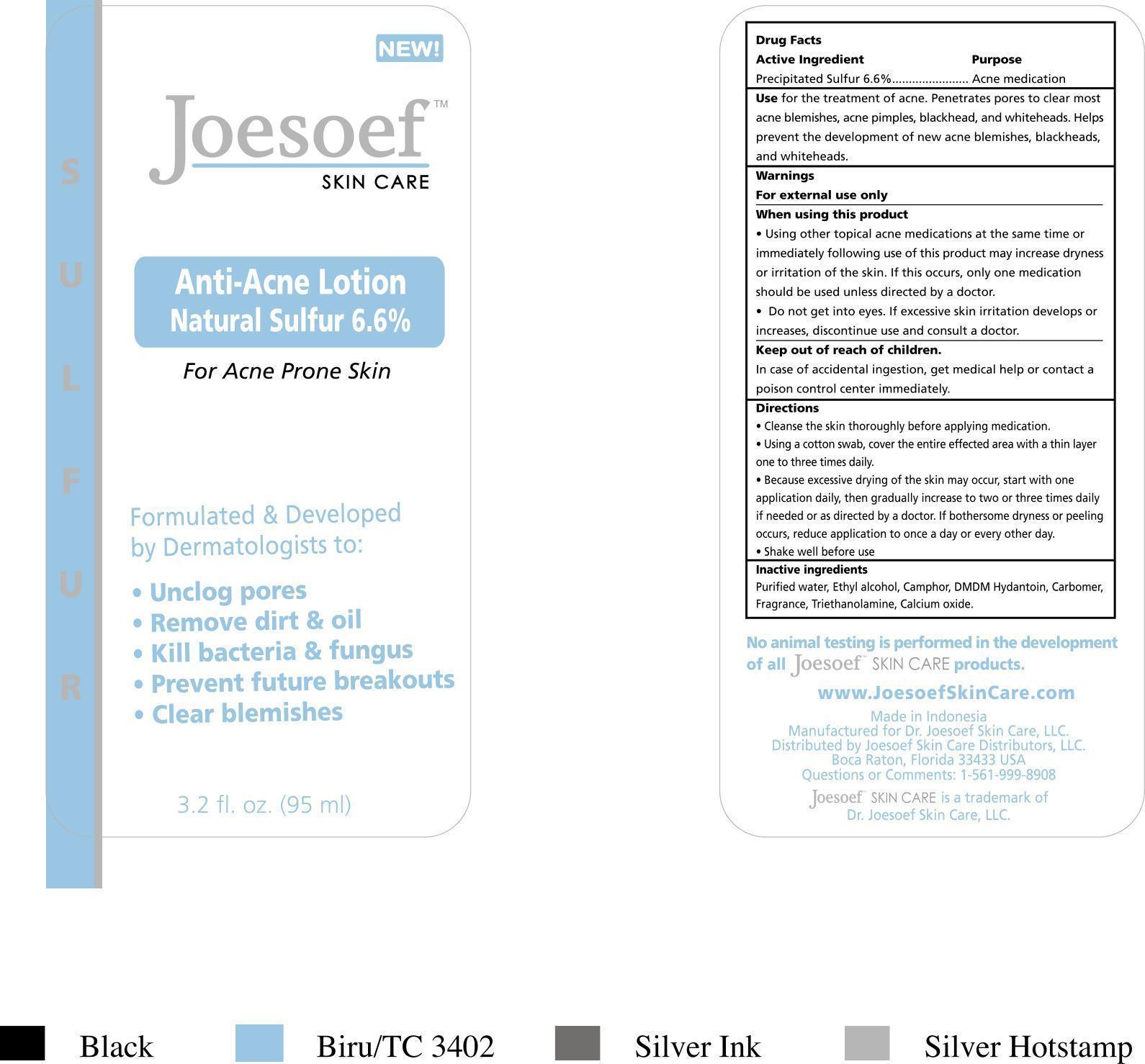 DRUG LABEL: Joesoef Skincare Anti Acne
NDC: 26050-113 | Form: LOTION
Manufacturer: PT Galenium Pharmasia Laboratories
Category: otc | Type: HUMAN OTC DRUG LABEL
Date: 20260105

ACTIVE INGREDIENTS: SULFUR 6.6 mg/100 mL
INACTIVE INGREDIENTS: WATER; ALCOHOL; DMDM HYDANTOIN; CARBOMER 1342; TRIETHANOLAMINE BENZOATE; LIME (CALCIUM OXIDE)

Anti-Acne Lotion

Drug Facts

Active Ingredients Purpose

Precipitated Sulfur 6.6%..............Acne medication

PURPOSE

Use for the treatment of acne. Penetrades pores to clear most acne blemishes, acne pimples, blackhead, and whiteheads. Helps prevent the development of new acne blemishes, blackheads, and whiteheads.

Keep out of reach of children.

In case of incidental ingestion, get medical help or contact a poison control center immediately.

Directions

- Cleanse the skin thoroughly before applying medication.
- Using a cotton swab, cover the entire effected area with a thin layer one to three times daily.
- Because excessive drying of the skim may occur, start with one application daily, then gradually increase to two or three times daily if needed or as directed by a doctor. If bothersome dryness or peeling occurs, reduce application to once a day or every other day.
- Shake well before use

Warnings

For external use only

When using this product

- Using other topical acne medications at the same time or immediately following use of this product may increase dryness or irritation of the skin. If this occurs, only one medication should be used unless directed by a doctor.
- Do not get into eyes. If excessive skin irridation develops or increases, discontinue use and consult a doctor.

Inactive ingredients

Purified water, Ethyl alcohol, DMDM Hydantoin, Cabomer, Fragrance, Triethanolamine, Calcium oxide.